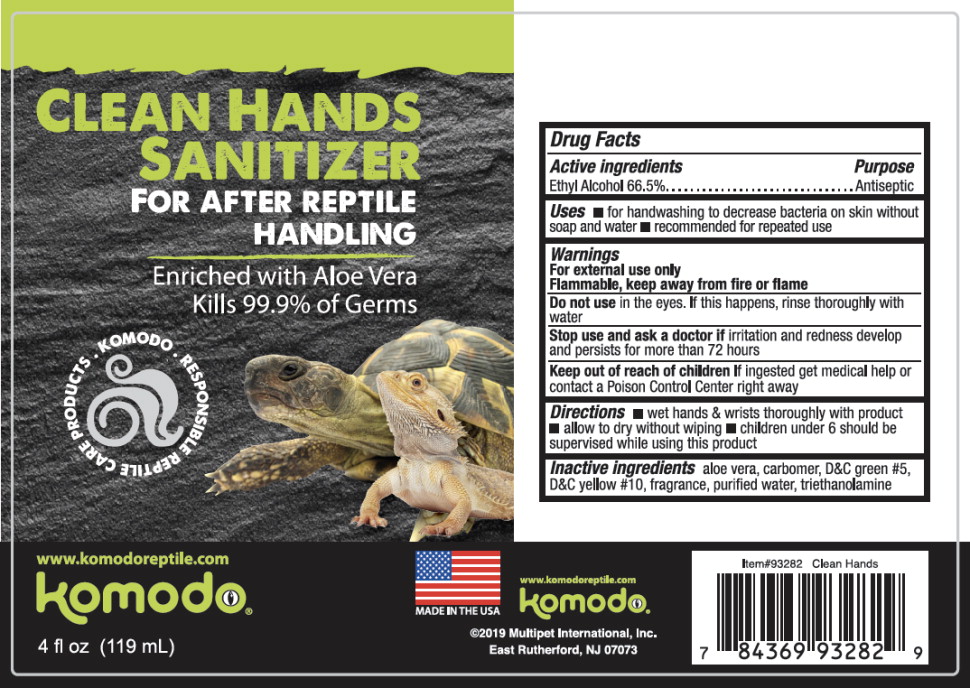 DRUG LABEL: Clean Hands Sanitizer
NDC: 73364-1111 | Form: GEL
Manufacturer: Multipet International Inc.
Category: otc | Type: HUMAN OTC DRUG LABEL
Date: 20191014

ACTIVE INGREDIENTS: alcohol 665 mL/1 L
INACTIVE INGREDIENTS: aloe vera leaf; CARBOMER INTERPOLYMER TYPE A (ALLYL SUCROSE CROSSLINKED); D&C GREEN NO. 5; D&C YELLOW NO. 10; water; trolamine

Drug Facts

Active ingredient

Ethyl Alcohol 66.5%

Purpose

Antiseptic

Uses

- for handwashing to decrease bacteria on skin without soap and water
- recommended for repeated use

Warnings

For external use only

Flammable, keep away from fire or flame

Do not use in the eyes. If this happens, rinse thoroughly with water

Stop use and ask a doctor if irritation and redness develop and persists for more than 72 hours

Keep out of reach of children

If ingested get medical help or contact a Poison Control Center right away

Directions

- wet hands & wrists thoroughly with product
- allow to dry without wiping
- children under 6 should be supervised while using this product

Inactive ingredients

aloe vera, carbomer, D&C green #5, D&C yellow #10, fragrance, purified water, triethanolamine

Principal Display Panel – 119 mL Bottle Label

CLEAN HANDS SANITIZER

FOR AFTER REPTILE
HANDLING

Enriched with Aloe Vera

Kills 99.9% of Germs

KOMODO RESPONSIBLE REPTILE CARE PRODUCTS

www.komodoreptile.com

komodo®

4 fl oz (119 mL)